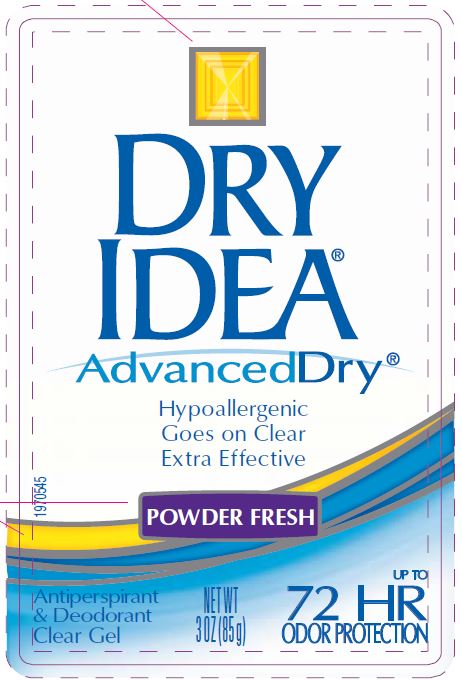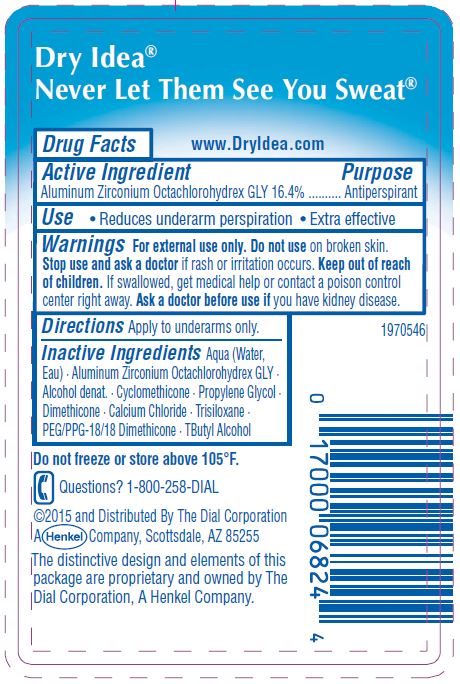 DRUG LABEL: Dry Idea Antiperspirant
NDC: 54340-291 | Form: GEL
Manufacturer: Henkel Corporation
Category: otc | Type: HUMAN OTC DRUG LABEL
Date: 20200212

ACTIVE INGREDIENTS: ALUMINUM ZIRCONIUM OCTACHLOROHYDREX GLY 16.4 g/100 g
INACTIVE INGREDIENTS: WATER 46.9 g/100 g

Dry Idea Antiperspirant Gel - Powder Fresh

Active Ingredient

Aluminum Zirconium Octachlorohydrex GLY 16.4%

Purpose

Antiperspirant

Use

• Reduces underarm perspiration • Extra effective

Warnings

For external use only. Do not use on broken skin.

Stop use and ask a doctor

if rash or irritation occurs.

Keep out of reach of children.

If swallowed, get medical help or contact a poison control center right away.

Ask a doctor before use if

you have kidney disease.

Directions

Apply to underarms only.

Inactive Ingredients

Aqua (Water, Eau) • Aluminum Zirconium Octachlorohydrex GLY • Alcohol Denat. • Cyclomethicone • Propylene Glycol • Dimethicone • Calcium Chloride • Trisiloxane • PEG/PPG-18/18 Dimethicone • TButyl Alcohol

STORAGE AND HANDLING

Do not freeze or store above 105⁰F

Questions? 1-800-258-DIAL